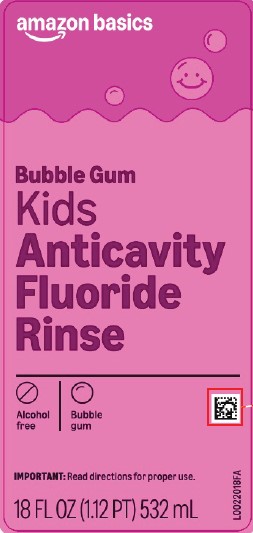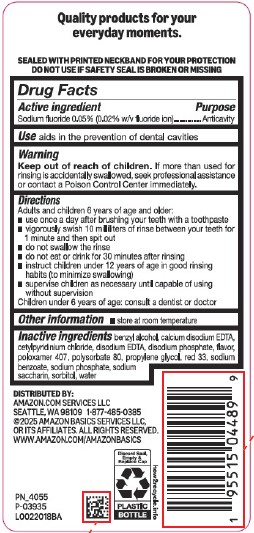 DRUG LABEL: Anticavity Rinse
NDC: 72288-004 | Form: MOUTHWASH
Manufacturer: Amazon. com Services LLC
Category: otc | Type: HUMAN OTC DRUG LABEL
Date: 20260113

ACTIVE INGREDIENTS: SODIUM FLUORIDE 0.2 mg/1 mL
INACTIVE INGREDIENTS: BENZYL ALCOHOL; EDETATE CALCIUM DISODIUM ANHYDROUS; CETYLPYRIDINIUM CHLORIDE; EDETATE DISODIUM; SODIUM PHOSPHATE, DIBASIC, ANHYDROUS; POLOXAMER 407; POLYSORBATE 80; PROPYLENE GLYCOL; D&C RED NO. 33; SODIUM BENZOATE; SODIUM PHOSPHATE; SACCHARIN SODIUM; SORBITOL; WATER

Basics 004.002/004AE
Anticavity Fluoride Rinse, Bubble Gum

Claim

Quality products for your everyday moments.

Tamper Evident Statement

SEALED WITH PRINTED NECKBAND FOR YOUR PROTECTION

DO NOT USE IF SAFETY SEAL IS BROKEN OR MISSING

Active ingredient

Sodium Fluoride 0.05% (0.02% w/v fluoride ion)

Purpose

Anticavity

Use

aids in the prevention of dental cavities

Warnings

for this product

Keep out of reach of children.

If more than used for rinsing is accidentally swallowed, seek professional assistance or contact a Poison Control Center immediately.

Directions

Adults and children 6 year of age and older:

- use once a day after brushing your teeth with a toothpaste
- vigorously swish 10 milliliters of rinse between your teeth for 1 minute and then spit out
- do not swallow the rinse
- do not eat or drink for 30 minutes after rinsing
- instruct children under 12 years of age in good rinsing habits (to minimize swallowing)
- supervise children as necessary until capable of using without supervision

Children under 6 year of age: consult a dentist or doctor

Other information

- store at room temperature

Inactive ingredients

benzyl alcohol, calcium disodium EDTA, cetylpyridinium chloride, disodium EDTA, disodium phosphate, flavor, poloxamer 407, polysorbate 80, propylene glycol, red 33, sodium benzoate, sodium phosphate, sodium saccharin, sorbitol, water

Adverse reactions

DISTRIBUTED BY:

Amazon.com Services, LLC

Seattle, WA 98109 1-877-485-0385

©2025 Amazon Basics Services LLC, or its affilates. All rights reserved.

www.amazon.com/amazonbasics

Discard Seal, Empty & Replace Cap

PLASTIC BOTTLE

how2recycle.info

principal display panel

amazon basics

Bubble Gum

Kids Anticavity Fluoride Rinse

Alcohol Free

Bubble Gum

IMPORTANT: READ DIRECTIONS FOR PROPER USE

18 FL OZ (1.12 PT) 532 mL